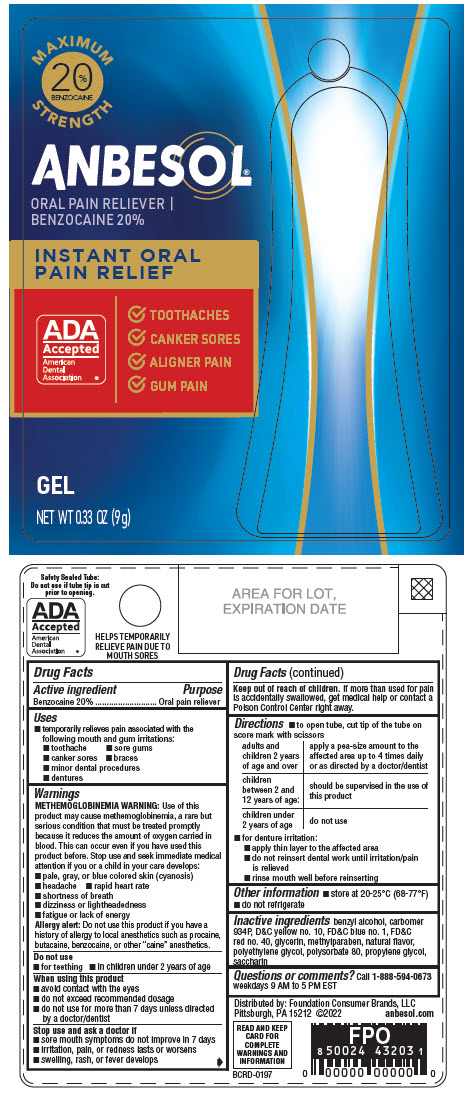 DRUG LABEL: Anbesol
NDC: 80070-220 | Form: GEL
Manufacturer: Foundation Consumer Brands
Category: otc | Type: HUMAN OTC DRUG LABEL
Date: 20250219

ACTIVE INGREDIENTS: BENZOCAINE 200 mg/1 g
INACTIVE INGREDIENTS: BENZYL ALCOHOL; CARBOMER HOMOPOLYMER TYPE B (ALLYL PENTAERYTHRITOL OR ALLYL SUCROSE CROSSLINKED); D&C YELLOW NO. 10; FD&C BLUE NO. 1; FD&C RED NO. 40; GLYCERIN; METHYLPARABEN; POLYETHYLENE GLYCOL, UNSPECIFIED; POLYSORBATE 80; PROPYLENE GLYCOL; SACCHARIN

Anbesol®
Maximum Strength

Drug Facts

Active ingredient

Benzocaine 20%

Purpose

Oral pain reliever

Uses

- temporarily relieves pain associated with the following mouth and gum irritations:
  - toothache
  - sore gums
  - canker sores
  - braces
  - minor dental procedures
  - dentures

Warnings

METHEMOGLOBINEMIA WARNING

Use of this product may cause methemoglobinemia, a rare but serious condition that must be treated promptly because it reduces the amount of oxygen carried in blood. This can occur even if you have used this product before. Stop use and seek immediate medical attention if you or a child in your care develops:

- pale, gray, or blue colored skin (cyanosis)
- headache
- rapid heart rate
- shortness of breath
- dizziness or lightheadedness
- fatigue or lack of energy

Allergy alert

Do not use this product if you have a history of allergy to local anesthetics such as procaine, butacaine, benzocaine, or other "caine" anesthetics.

Do not use

- for teething
- in children under 2 years of age

When using this product

- avoid contact with the eyes
- do not exceed recommended dosage
- do not use for more than 7 days unless directed by a doctor/dentist

Stop use and ask a doctor if

- sore mouth symptoms do not improve in 7 days
- irritation, pain, or redness lasts or worsens
- swelling, rash, or fever develops

Keep out of reach of children.If more than used for pain is accidentally swallowed, get medical help or contact a Poison Control Center right away.

Directions

- to open tube, cut tip of the tube on score mark with scissors
  adults and children 2 years of age and over | apply a pea-size amount to the affected area up to 4 times daily or as directed by a doctor/dentist
  children under 12 years of age | adult supervision should be given in the use of this product
  children under 2 years of age | do not use
- for denture irritation:
  - apply thin layer to the affected area
  - do not reinsert dental work until irritation/pain is relieved
  - rinse mouth well before reinserting

Other information

- store at 20-25°C (68-77°F)
- do not refrigerate

Inactive ingredients

benzyl alcohol, carbomer 934P, D&C yellow no. 10, FD&C blue no. 1, FD&C red no. 40, glycerin, methylparaben, natural flavor, polyethylene glycol, polysorbate 80, propylene glycol, saccharin

Questions or comments?

Call 1-888-594-0673weekdays 9 AM to 5 PM EST

Distributed by: Foundation Consumer Brands, LLC
Pittsburgh, PA 15212

PRINCIPAL DISPLAY PANEL - 9 g Tube Blister Pack

MAXIMUM STRENGTH

20% Benzocaine

Anbesol®
Oral Pain Reliever/Benzocaine 20%

Instant Oral
Pain Relief

ADA Accepted

American Dental Association

- Toothaches
- Canker Sores
- Aligner Pain
- Gum Pain

GEL

NET WT 0.33 OZ (9 g)